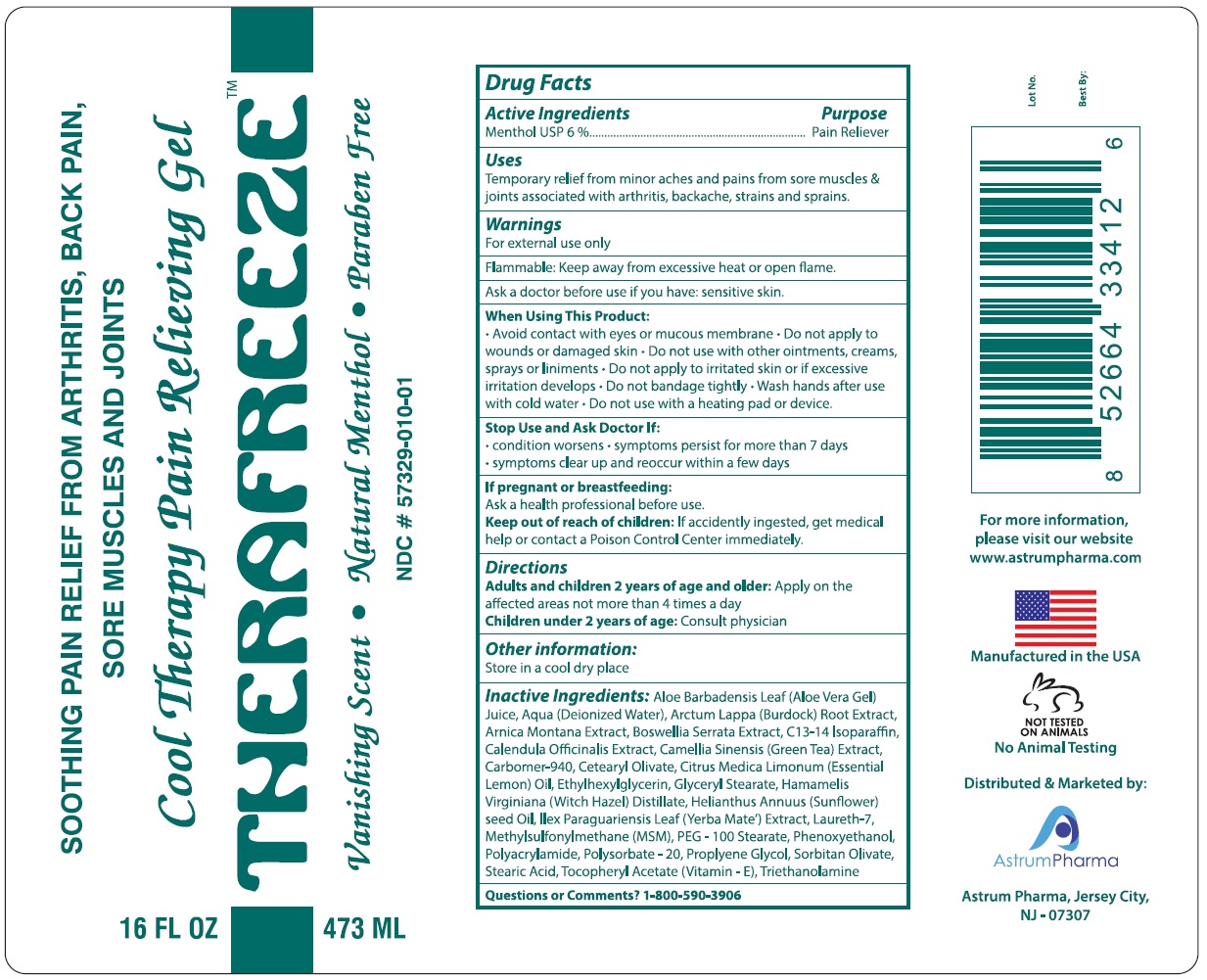 DRUG LABEL: THERAFREEZE
NDC: 57329-010 | Form: GEL
Manufacturer: Astrum Pharma
Category: otc | Type: HUMAN OTC DRUG LABEL
Date: 20130808

ACTIVE INGREDIENTS: MENTHOL 60 mg/1 mL
INACTIVE INGREDIENTS: ALOE VERA LEAF; WATER; ARCTIUM LAPPA ROOT; ARNICA MONTANA FLOWER; INDIAN FRANKINCENSE; C13-14 ISOPARAFFIN; CALENDULA OFFICINALIS FLOWER; GREEN TEA LEAF; CARBOMER HOMOPOLYMER TYPE C (ALLYL PENTAERYTHRITOL CROSSLINKED); CETEARYL OLIVATE; CITRUS LIMON FRUIT OIL; ETHYLHEXYLGLYCERIN; GLYCERYL MONOSTEARATE; WITCH HAZEL; SUNFLOWER OIL; ILEX PARAGUARIENSIS LEAF; LAURETH-7; DIMETHYL SULFONE; PEG-100 STEARATE; PHENOXYETHANOL; POLYACRYLAMIDE (10000 MW); POLYSORBATE 20; PROPYLENE GLYCOL; SORBITAN OLIVATE; STEARIC ACID; .ALPHA.-TOCOPHEROL ACETATE; TROLAMINE

THERAFREZZETM

Drug Facts

Active Ingredients

Menthol USP 6%

Purpose

Pain Reliever

Uses

Temporary relief from minor aches and pains from sore muscles & joints associated with arthritis, backache, strains and sprains.

Warnings

For external use only.

Flammable: Keep away from excessive heat or open flame.

Ask a doctor before use if you have: sesnitive skin.

When Using This Product:

- Avoid contact with eyes or mucous membrane.
- Do not apply to wounds or damaged skin.
- Do not use with other ointments, creams, sprays or liniments.
- Do not apply to irritated skin or if excessive irritation develops.
- Do not bandage tightely.
- Wash hands after use with cold water.
- Do not use with a heating pad or device.

Stop Use and Ask Doctor if

- conditions worsen.
- symptoms persist for more than 7 days.
- symptoms clear up and occur again within a few days.

If pregnant or breastfeeding:

Ask a health professional before use.

Keep out of reach of children:If accidently ingested, get medical help or contact a Poison Control Center immediately.

Directions

Adults and children 12 years of age and older: Apply on the affacted areas not more than 4 times a day.

Children under 2 years of age: Consult physician.

Other information

Store in cool dry place.

Inactive ingredients:

Aloe Barbadensis Leaf (Aloe Vera Gel) Juice, Aqua (Deionized Water), Arctum Lappa (Burdock) Root Extract, Arnica Montana Extract, Boswellia Serrata Extract, C13-14 Isoparaffin, Calendula Officinalis Extract, Camellia Sinensis (Green Tea) Extract, Carbomer-940, Cetearyl Oliviate, Citrus Media Limonum (Essential Lemon) Oil, Ethylhexylglycerin, Glyceryl Stearate, Hamamelis Virginiana (Witch Hazel) Distillate, Helianthus Annuus (Sunflower) seed Oil, IIex Paraguariensis Leaf (Yerba Mate') Extract, Laureth-7, Methylsulfonylmethane (MSM), PEG - 100 Stearate, Phenoxyethanol, Polyacrylmide, Polysorbate - 20, Propylene Glycol, Sorbitan Olivate, Stearic Acid, Tocopheryl Acetate (Vitamin - E), Triethanolamine.

For more information,
please visit our website
www.astrumpharma.com

Manufactured in the USA

No Animal Testing

Distributed and Marketed by:
Astrum Pharma, Jersey City,
NJ-07307

Principal Display Panel

SOOTHING PAIN RELIEF FROM ARTHRITIS, BACK PAIN,
SORE MUSCLES AND JOINTS

Cool Therapy Pain Relieving Gel

THERAFREEZETM

Vanishing Scent •Natural Menthol •Paraben Free

NDC # 57329-010-01

16 FL OZ

473 ML